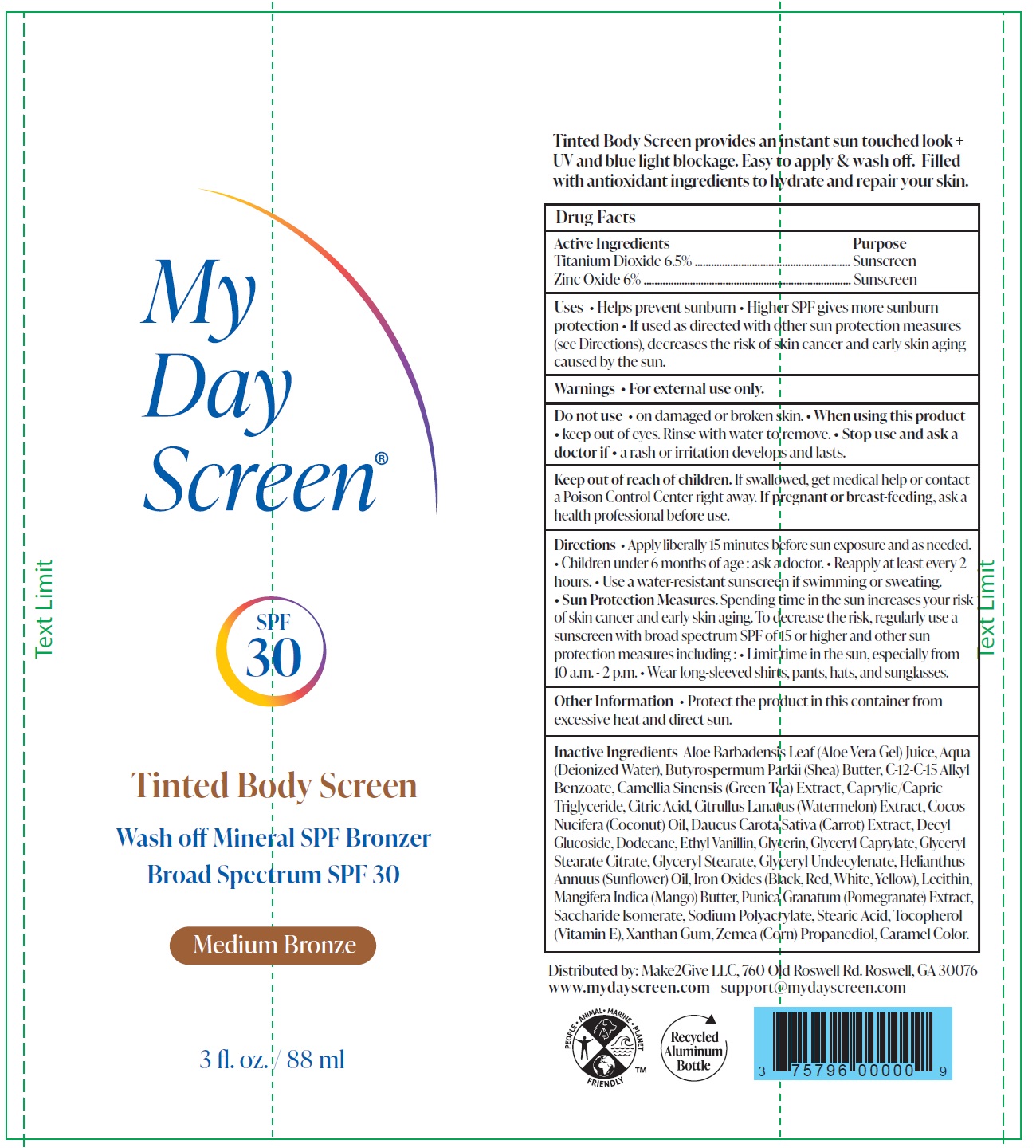 DRUG LABEL: Tinted Body Screen Medium Bronze
NDC: 75796-017 | Form: LOTION
Manufacturer: Make2Give LLC
Category: otc | Type: HUMAN OTC DRUG LABEL
Date: 20240806

ACTIVE INGREDIENTS: TITANIUM DIOXIDE 65 mg/1 mL; ZINC OXIDE 60 mg/1 mL
INACTIVE INGREDIENTS: ALOE VERA LEAF; WATER; SHEA BUTTER; ALKYL (C12-15) BENZOATE; GREEN TEA LEAF; MEDIUM-CHAIN TRIGLYCERIDES; CITRIC ACID MONOHYDRATE; WATERMELON; COCONUT; CARROT; DECYL GLUCOSIDE; ETHYL VANILLIN; GLYCERIN; GLYCERYL CAPRYLATE; GLYCERYL STEARATE CITRATE; GLYCERYL MONOSTEARATE; HELIANTHUS ANNUUS FLOWERING TOP; FERROSOFERRIC OXIDE; FERRIC OXIDE RED; FERRIC OXIDE YELLOW; MANGO; POMEGRANATE; SACCHARIDE ISOMERATE; SODIUM CITRATE; STEARIC ACID; .ALPHA.-TOCOPHEROL; XANTHAN GUM; CORN

Tinted Body Screen Medium Bronze

Active Ingredients

Titanium Dioxide 6.5%

Zinc Oxide 6%

Purpose

Sunscreen

Uses

• Helps prevent sunburn • Higher SPF gives more sunburn protection • If used as directed with other sun protection measures (see Directions), decreases the risk of skin cancer and early skin aging caused by the sun.

Warnings

• For external use only.

Do not use

• on damaged or broken skin.

When using this product

• keep out of eyes. Rinse with water to remove.

Stop use and ask a doctor if

• a rash or irritation develops and lasts.

Keep out of reach of children.

If swallowed, get medical help or contact a Poison Control Center right away.

If pregnant or breast-feeding,

ask a health professional before use.

Directions

• Apply liberally 15 minutes before sun exposure and as needed. • Children under 6 months of age : ask a doctor. • Reapply at least every 2 hours. • Use a water-resistant sunscreen if swimming or sweating. • Sun Protection Measures.Spending time in the sun increases your risk of skin cancer and early skin aging. To decrease the risk, regularly use a sunscreen with broad spectrum SPF of 15 or higher and other sun protection measures including : • Limit time in the sun, especially from 10 a.m. - 2 p.m. • Wear long-sleeved shirts, pants, hats, and sunglasses.

Other Information

• Protect the product in this container from excessive heat and direct sun.

Inactive ingredients

Aloe Barbadensis Leaf (Aloe Vera Gel) Juice, Aqua (Deionized Water), Butyrospermum Parkii (Shea) Butter, C-12-C-15 Alkyl Benzoate, Camellia Sinensis (Green Tea) Extract, Caprylic/Capric Triglyceride, Citric Acid, Citrullus Lanatus (Watermelon) Extract, Cocos Nucifera (Coconut) Oil, Daucus Carota Sativa (Carrot) Extract, Decyl Glucoside, Dodecane, Ethyl Vanillin, Glycerin, Glyceryl Caprylate, Glyceryl Stearate Citrate, Glyceryl Stearate, Glyceryl Undecylenate, Helianthus Annuus (Sunflower) Oil, Iron Oxides (Black, Red, White, Yellow), Lecithin, Mangifera Indica (Mango) Butter, Punica Granatum (Pomegranate) Extract, Saccharide lsomerate, Sodium Polyacrylate, Stearic Acid, Tocopherol (Vitamin E), Xanthan Gum, Zemea (Corn) Propanediol, Caramel Color.